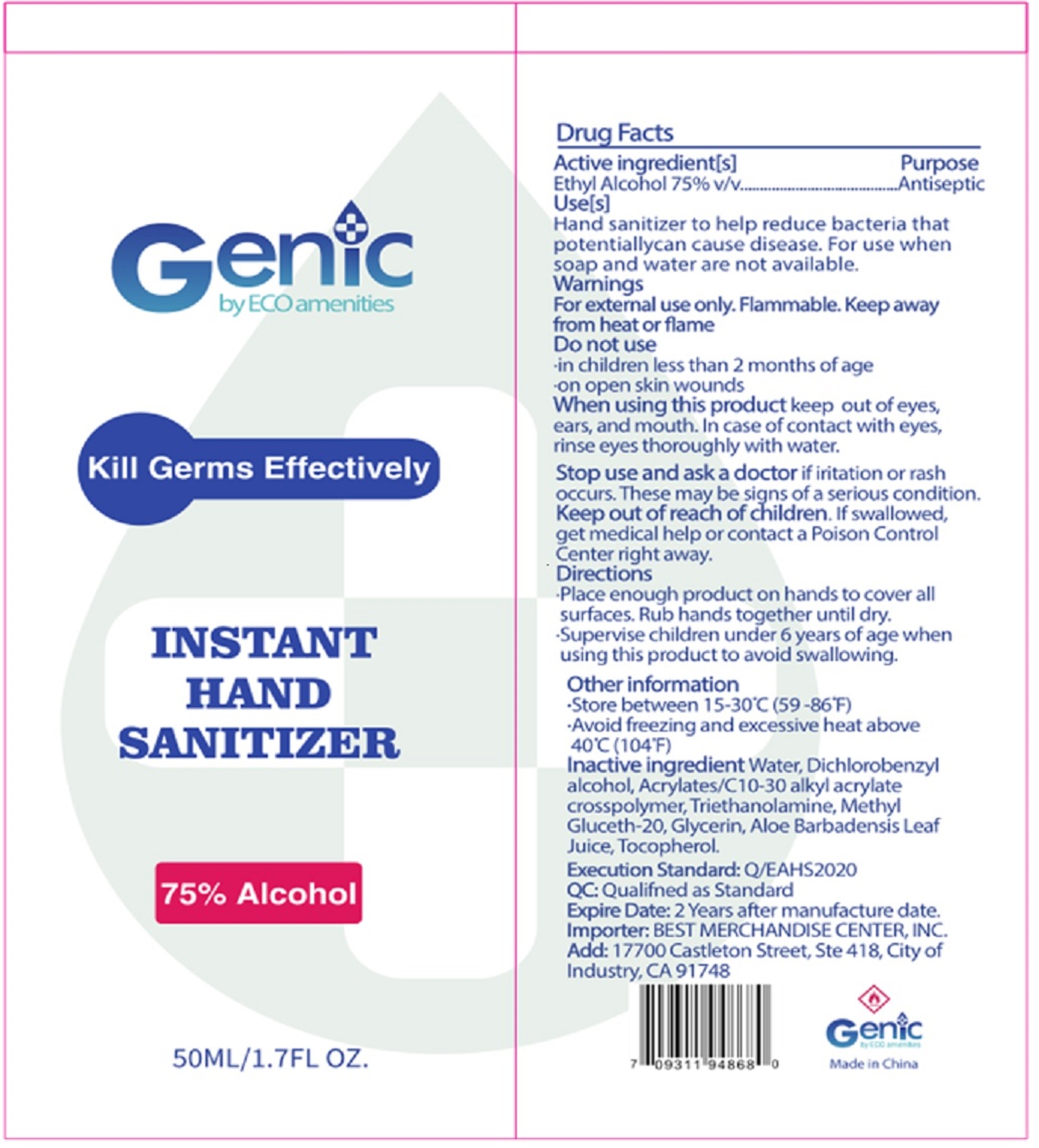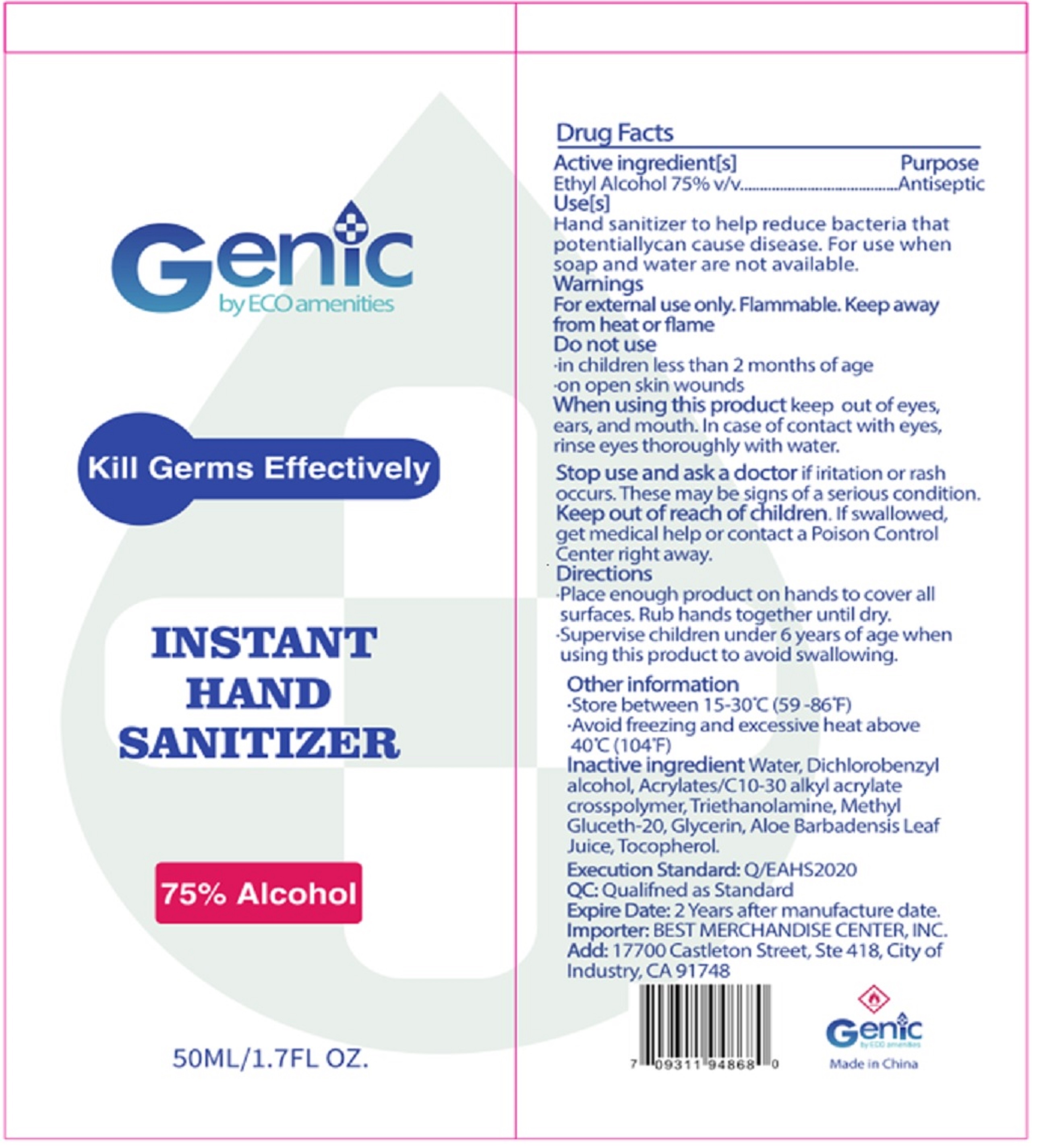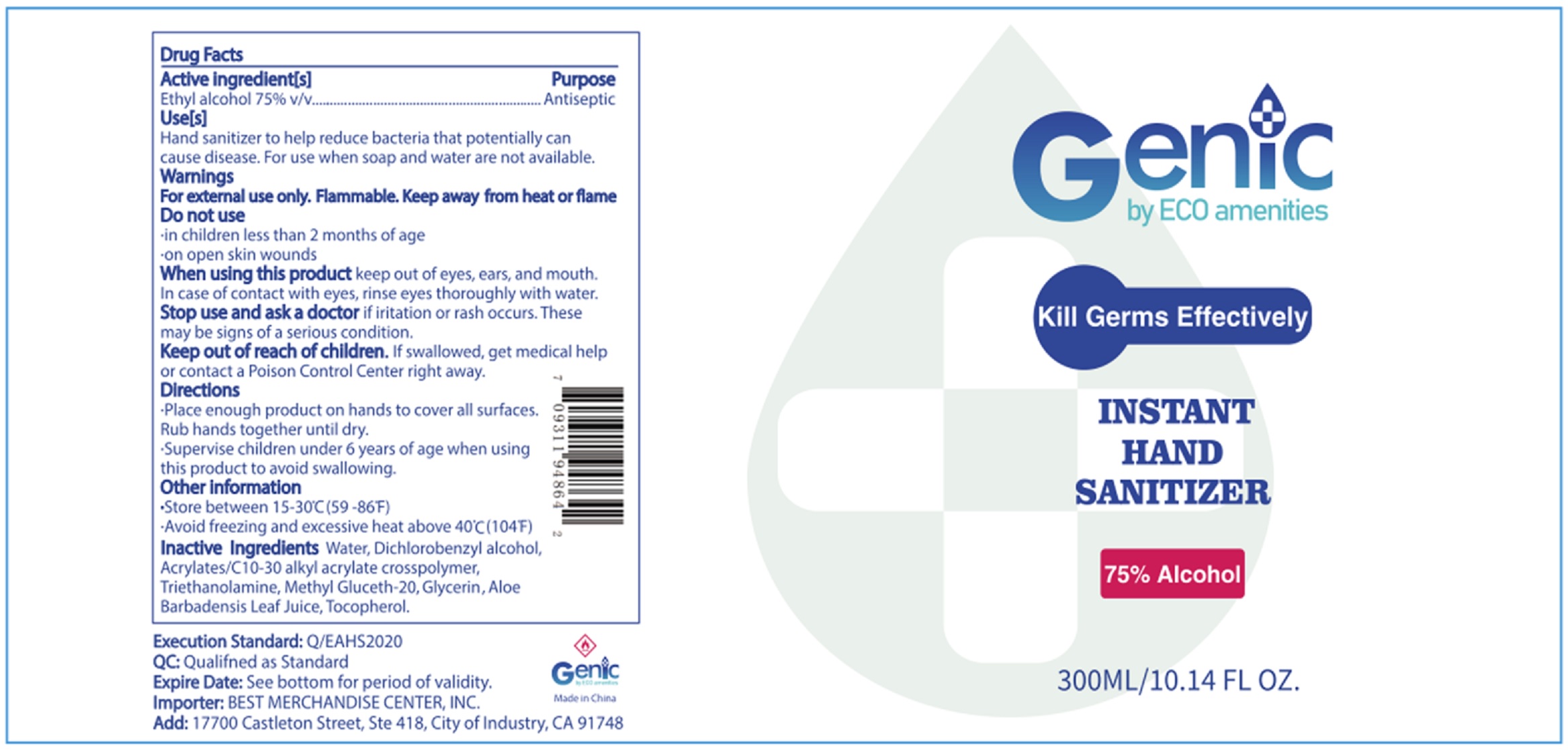 DRUG LABEL: Genic by Eco Amenities Hand Sanitizer
NDC: 77849-001 | Form: GEL
Manufacturer: Yanghzou Eco-Amenities CO., Ltd
Category: otc | Type: HUMAN OTC DRUG LABEL
Date: 20200618

ACTIVE INGREDIENTS: ALCOHOL 0.75 mL/1 mL
INACTIVE INGREDIENTS: WATER; DICHLOROBENZYL ALCOHOL; CARBOMER INTERPOLYMER TYPE A (ALLYL SUCROSE CROSSLINKED); TROLAMINE; METHYL GLUCETH-20; GLYCERIN; ALOE VERA LEAF; TOCOPHEROL

Genic by Eco Amenities Hand Sanitizer

Active ingredient[s]

Ethyl alcohol 75% v/v

Purpose

Antiseptic

Use[s]

Hand sanitizer to help reduce bacteria that potentially can cause disease. For use when soap and water are not available.

Warnings

For external use only. Flammable. Keep away from heat or flame

Do not use

- in children less than 2 months of age
- on open skin wounds

When using this product

keep out of eyes, ears, and mouth. In case of contact with eyes, rinse eyes thoroughly with water.

Stop use and ask a doctor

if irritation or rash occurs. These may be signs of a serious condition.

Keep out of reach of children.

If swallowed, get medical help or contact a Poison Control Center right away.

Directions

- Place enough product on hands to cover all surfaces. Rub hands together until dry.
- Supervise children under 6 years of age when using this product to avoid swallowing.

Other information

- Store between 15-30°C (59-86°F)
- Avoid freezing and excessive heat above 40°C (104°F)

Inactive ingredient

Water, Dichlorobenzyl alcohol, Acrylates/C10-30 alkyl acrylate crosspolymer, Triethanolamine, Methyl Gluceth-20, Glycerin, ALoe Barbadensis Leaf Juice, Tocopherol.